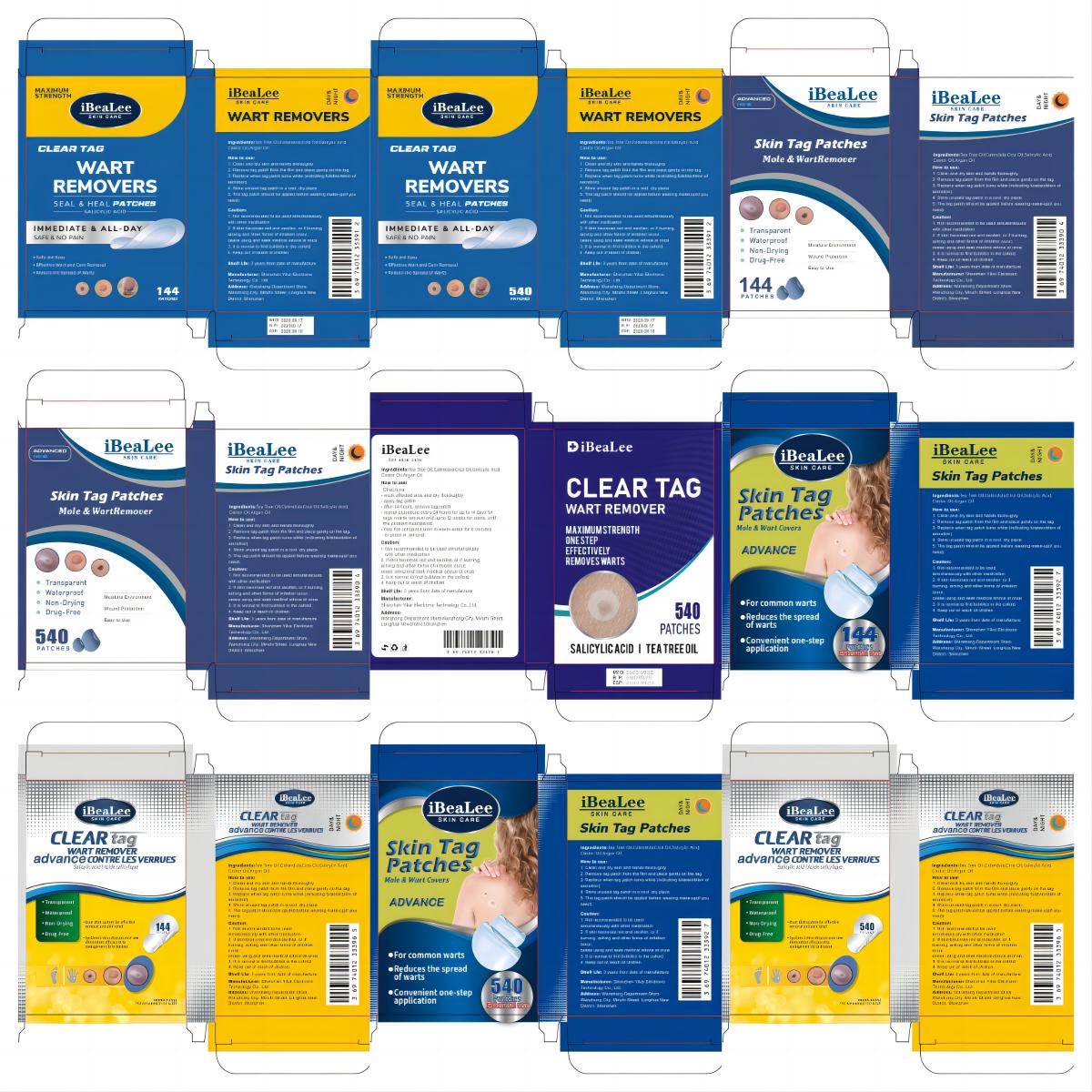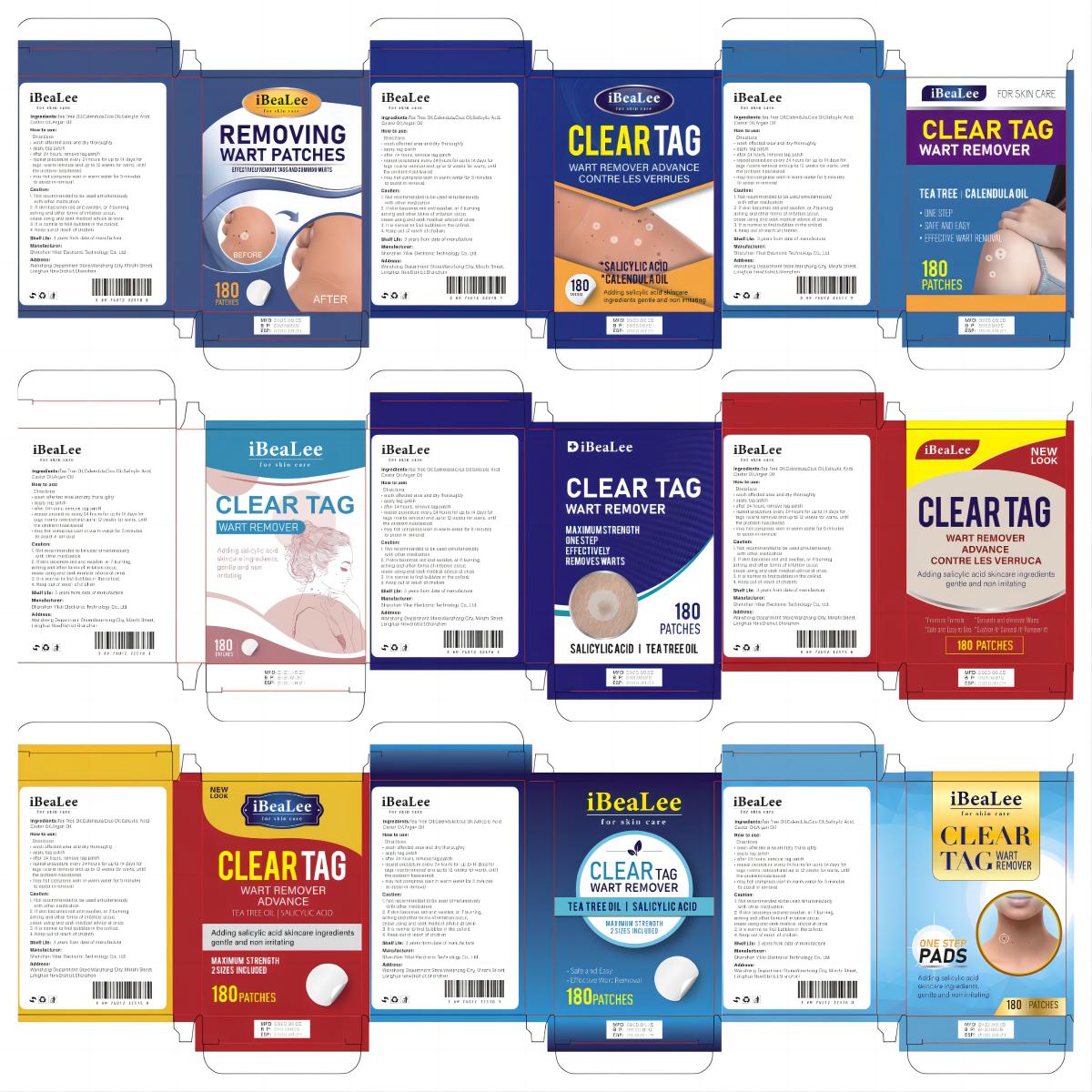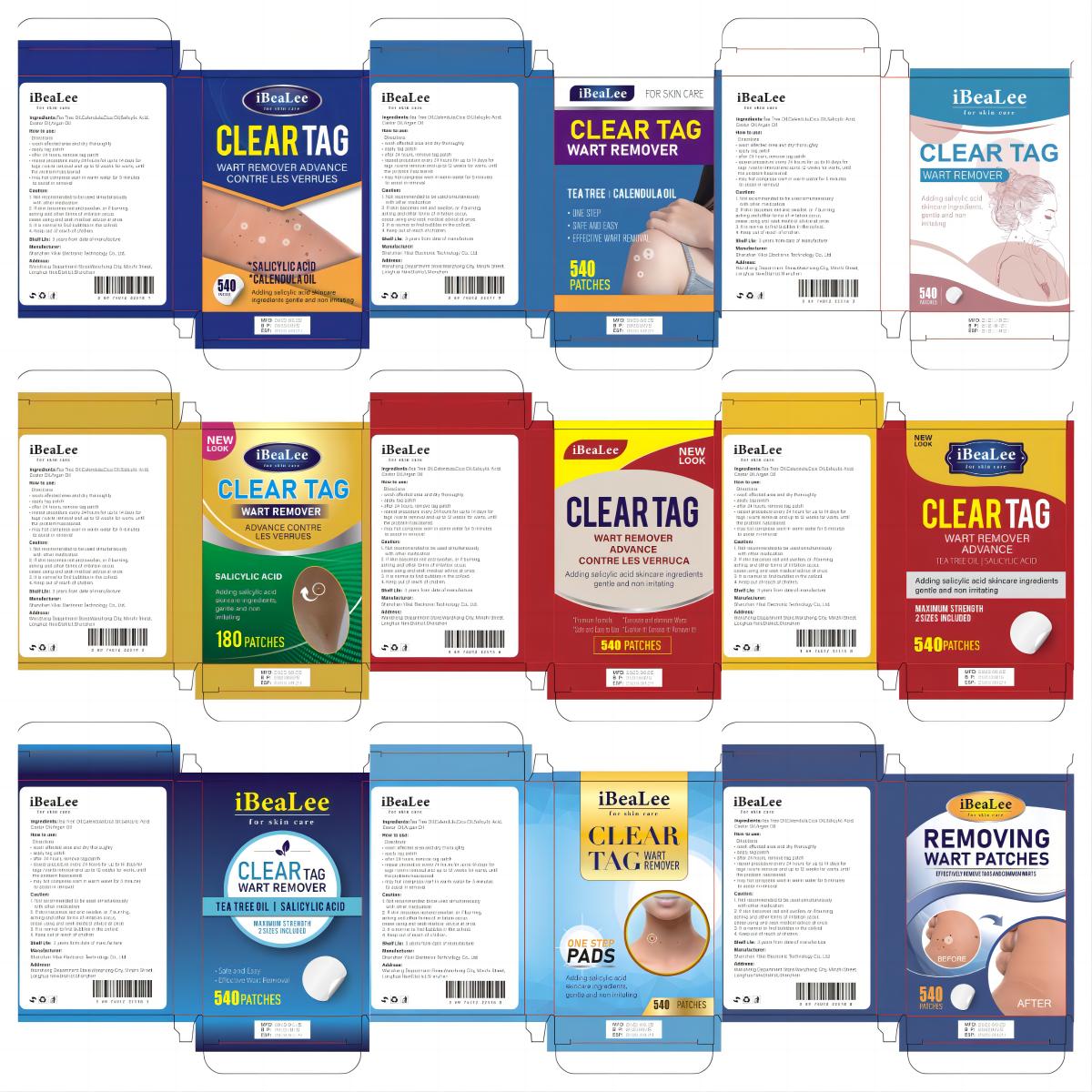 DRUG LABEL: iBeaLee WART REMOVER
NDC: 83675-014 | Form: PATCH
Manufacturer: Guangzhou Hanhai Trading Co., Ltd
Category: otc | Type: HUMAN OTC DRUG LABEL
Date: 20230927

ACTIVE INGREDIENTS: SALICYLIC ACID 40 g/100 1
INACTIVE INGREDIENTS: OITICICA OIL; TEA TREE OIL; CALENDULA OFFICINALIS FLOWER; CASTOR OIL; ARGAN OIL

Active Ingredient

Salicylic Acid 40%

Purpose

WART REMOVER

Use

How to use:
Directions
• wash affected area and dry thoroughly
• apply tag patch
• after 24 hours, remove tag patch
• repeat procedure every 24 hours for up to 14 days for
tags /warts removal and up to 12 weeks for warts, until
the problem hascleared.
• may hot compress wart in warm water for 5 minutes
to assist in removal

Warnings

Caution:
1. Not recommended to be used simuitaneously
with other medication.
2. If skin becomes red and swollen, or if burning,
aching and other forms of irritation occur,
cease using and seek medical advice at once.
3. It is normal to find bubbles in the colloid.
4. Keep out of reach of chidren.

Keep Oot Of Reach Of Children

Do not place this product within the reach of children

Do not use

If allergy occurs, please stop using it

Inactive ingredients

Tea Tree Oil,Calendula,Cica
Oil,Castor Oil,
Argan Oil

Directions

Apply gently to skin